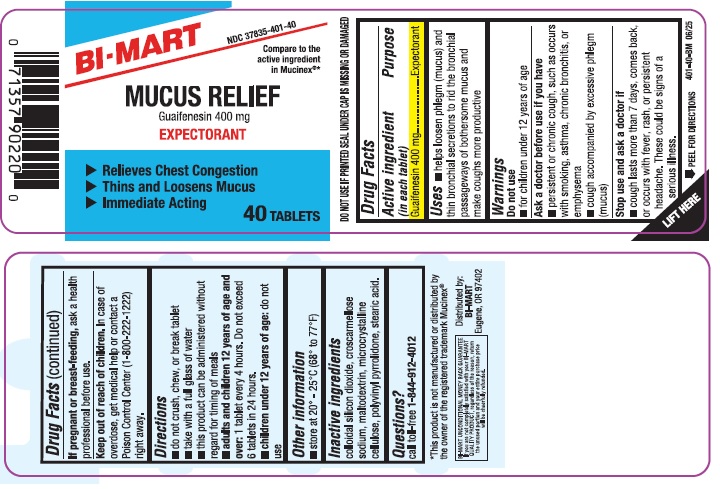 DRUG LABEL: Mucus Relief
NDC: 37835-401 | Form: TABLET
Manufacturer: Bi-Mart
Category: otc | Type: HUMAN OTC DRUG LABEL
Date: 20250501

ACTIVE INGREDIENTS: GUAIFENESIN 400 mg/1 1
INACTIVE INGREDIENTS: SILICON DIOXIDE; CROSCARMELLOSE SODIUM; MALTODEXTRIN; CELLULOSE, MICROCRYSTALLINE; POVIDONE; STEARIC ACID

Active ingredient (in each tablet)

Guaifenesin 400 mg

Purpose

Expectorant

Uses

- helps loosen phlegm (mucus) and thin bronchial secretions to rid the bronchial passageway of bothersome mucus and make coughs more productive

Warnings

Do not use

- for children under 12 years of age

Ask a doctor before use if you have

- persistent or chronic cough such as occurs with smoking, asthma, chronic bronchitis or emphysema
- cough accompanied by excessive phlegm (mucus)

Stop use and ask a doctor if

- cough lasts more than 7 days, comes back, or occurs with fever, rash, or persistent headache. These could be signs of a serious illness.

PREGNANCY OR BREAST FEEDING

If pregnant or breast-feeding, ask a health professional before use.

Keep out of reach of children.

In case of overdose, get medical help or contact a Poison Control Center (1-800-222-1222) right away.

Directions

- do not crush, chew, or break tablet
- take with a full glass of water
- this product can be administered without regard for timing of meals
- adults and children 12 years of age and over: 1 tablet every 4 hours. Do not exceed 6 tablets in 24 hours.
- children under 12 years of age: do not use

Other information

- store at 20-25°C (68-77°F)
- DO NOT USE IF PRINTED SEAL UNDER CAP IS MISSING OR DAMAGED

Inactive ingredients

colloidal silicon dioxide, croscarmellose sodium, maltodextrin, microcrystalline cellulose, polyvinyl pyrrolidone, stearic acid.

Questions?

call toll-free 1-844-912-4012

Distributed by:

BI-MART

Eugene, OR 97402